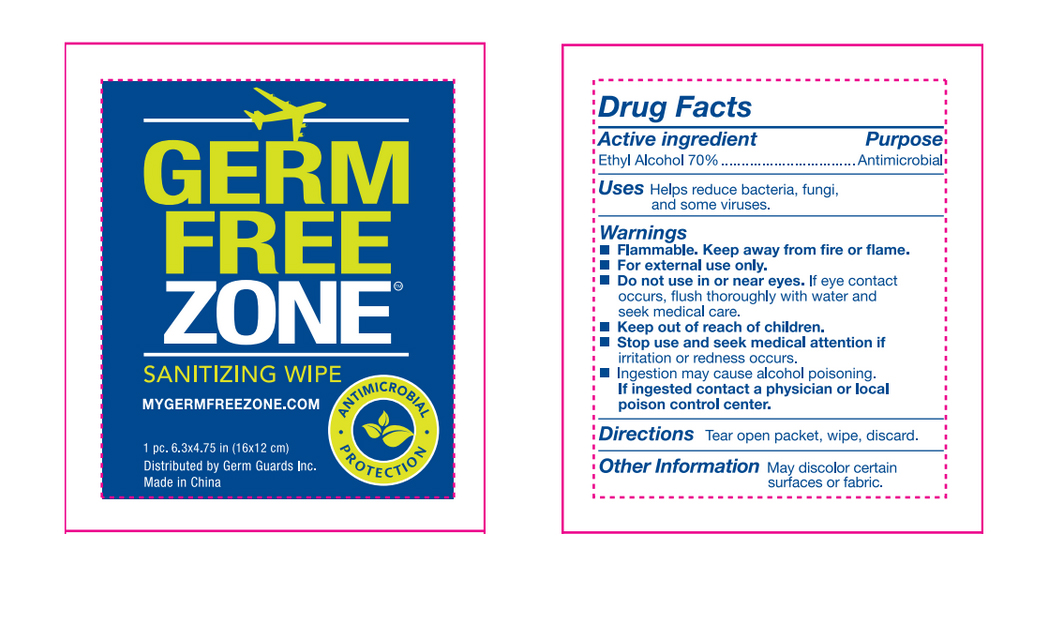 DRUG LABEL: Sanitizing Wipes
NDC: 71089-003 | Form: CLOTH
Manufacturer: Germ Guards Incorporated
Category: otc | Type: HUMAN OTC DRUG LABEL
Date: 20170823

ACTIVE INGREDIENTS: ALCOHOL 0.7 mL/0.7 mL
INACTIVE INGREDIENTS: WATER

Active Ingredient

Ethyl Alcohol 70% (v/v)

Purpose

Antimicrobial

Uses

Helps reduce bacteria, fungi, and some viruses

Warnings

Flammable, Keep away from fire or flame.

For External Use Only

Do not use in or near eyes. If eye contact occurs, flush thoroughly with water and seek medical care.

Stop use and seek medical attention if irritation or redness occurs

Ingestion may cause alcohol poisoning

Keep out of reach of children

Directions

Tear open packet, wipe, discard

Inactive Ingredients

Pure Water

Other Information

May discolor certain surfaces or fabric